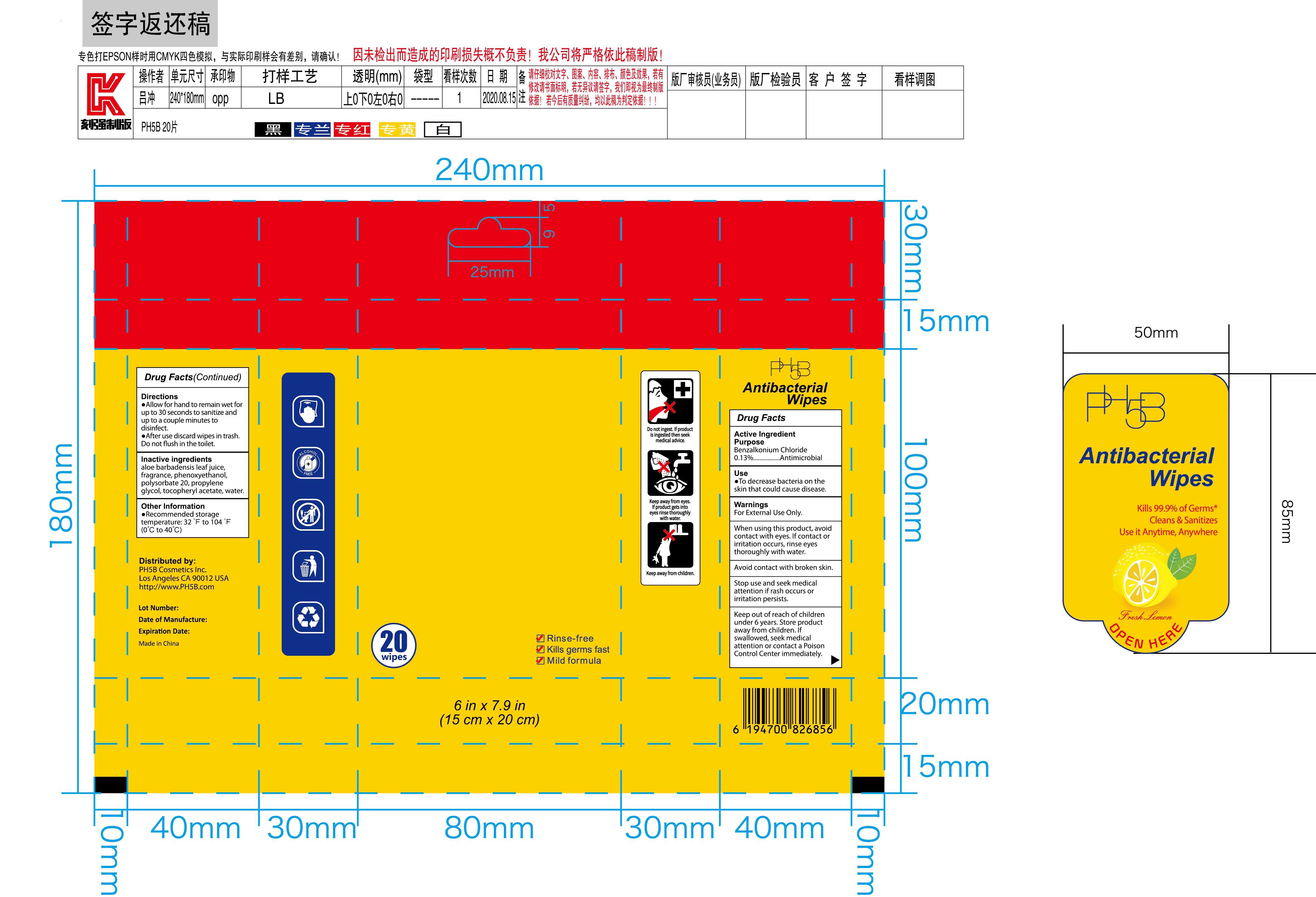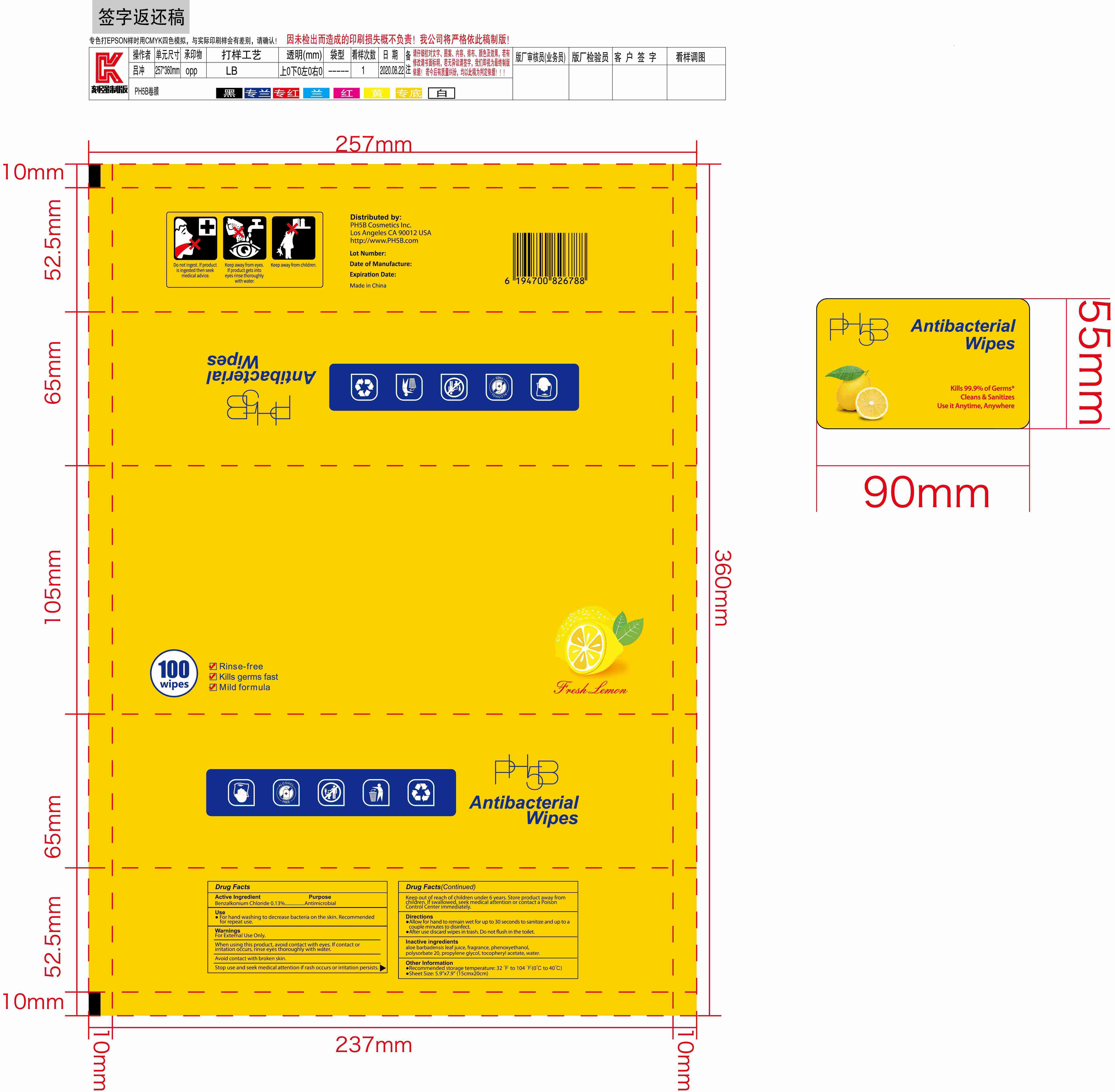 DRUG LABEL: Antibacterial wipes
NDC: 42003-204 | Form: CLOTH
Manufacturer: Zhejiang Jiayan Daily Commodity Co., Ltd
Category: otc | Type: HUMAN OTC DRUG LABEL
Date: 20220225

ACTIVE INGREDIENTS: BENZALKONIUM CHLORIDE 0.13 g/100 1
INACTIVE INGREDIENTS: ALOE VERA LEAF; CHAMOMILE; PHENOXYETHANOL; POLYSORBATE 20; ALPHA-TOCOPHEROL ACETATE; WATER; LEMON

42003-204
Antibacterial wipes

Active Ingredient(s)

Benzalkonium Chloride 0.13%

Purpose

Antimicrobial

Use

For hand washing to decrease bacteria on the skin. Recommended for repeat use.

Warnings

For External Use Only.

When using this product, avoid contact with eyes. If contact or irritation occurs, rinse eyes thoroughly with water.
Avoid contact with broken skin.

Stop use and seek medical attention if rash occurs or irritation persists

Keep out of reach of children under 6 years. Store product away from children. If swallowed, seek medical attention or contact a Poison Control Center immediately.

Do not use

/

When using this product, avoid contact with eyes. If contact or irritation occurs, rinse eyes thoroughly with water.
Avoid contact with broken skin.

Stop use and seek medical attention if rash occurs or irritation persists

Keep out of reach of children under 6 years. Store product away from children. If swallowed, seek medical attention or contact a Poison Control Center immediately.

Stop use and seek medical attention if rash occurs or irritation persists

Keep out of reach of children under 6 years. Store product away from children. If swallowed, seek medical attention or contact a Poison Control Center immediately.

Directions

Allow for hand to remain wet for up to 30 seconds to sanitize and up to a couple minutes to disinfect.
After use discard wipes in trash. Do not flush in the toilet.

Other information

Recommended storage temperature: 32°F to 104°F（0°C to 40°C)
Sheet Size: 5.9"x7.9" (15cm*20cm)

Inactive ingredients

aloe barbadensis leaf juice, fragrance, phenoxyethanol, polysorbate 20, propylene glycol, tocopheryl acetate, water.